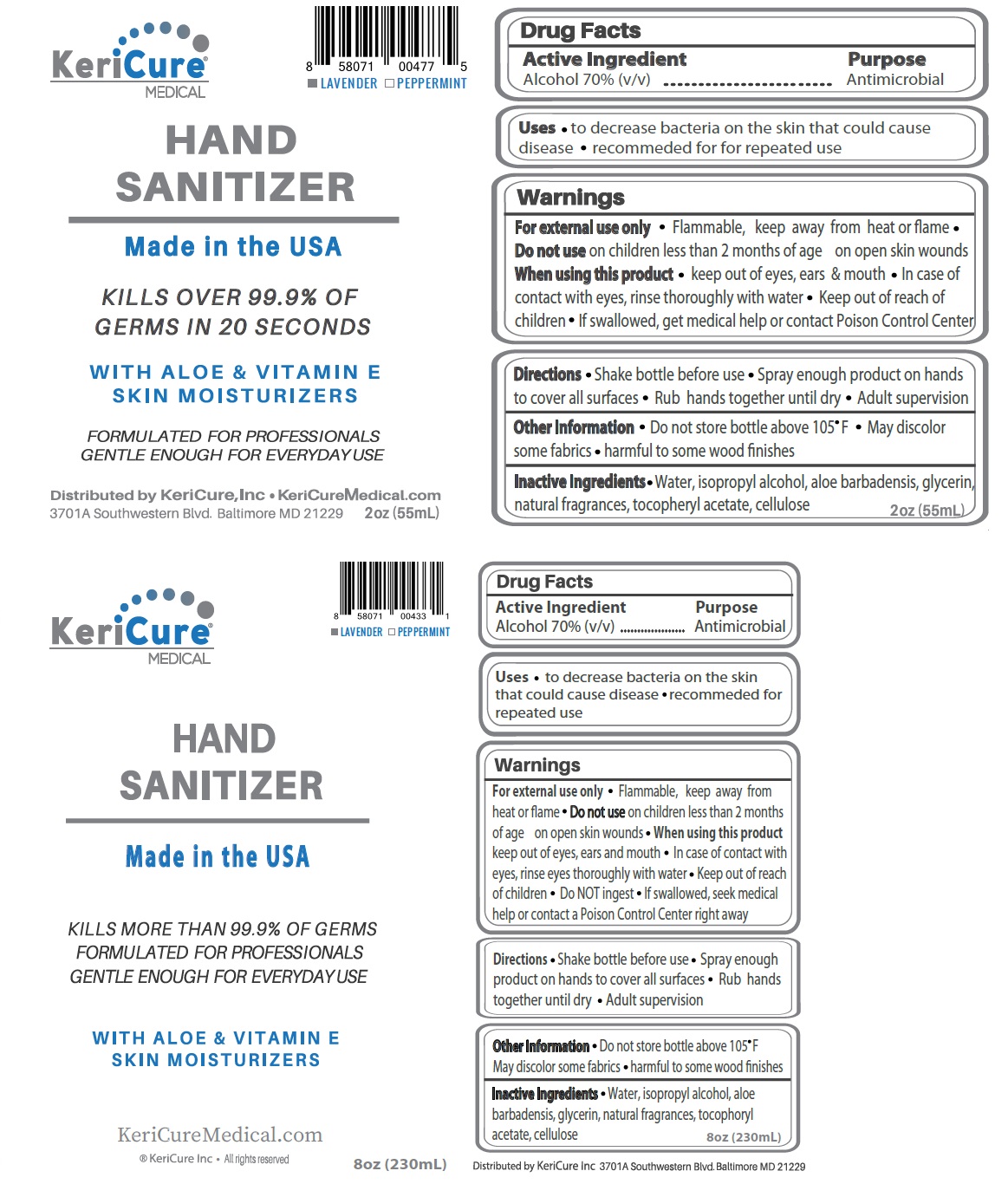 DRUG LABEL: KeriCure Hand Sanitizer
NDC: 78280-304 | Form: SPRAY
Manufacturer: Kericure Inc.
Category: otc | Type: HUMAN OTC DRUG LABEL
Date: 20250122

ACTIVE INGREDIENTS: ALCOHOL 70 mL/100 mL
INACTIVE INGREDIENTS: WATER; ISOPROPYL ALCOHOL; ALOE VERA LEAF; GLYCERIN; .ALPHA.-TOCOPHEROL ACETATE; HYDROXYETHYL CELLULOSE (2000 MPA.S AT 1%)

KeriCure® HAND SANITIZER

Active Ingredient

Alcohol 70% (v/v)

Purpose

Antimicrobial

INDICATIONS AND USAGE

Uses • to decrease bacteria on the skin that could cause disease • recommended for repeated use

Warnings

For external use only • Flammable, keep away from heat or flame • Do not use on children less than 2 month of age on open skin wounds • When using this product keep out of eyes, ears and mouth • In case of contact with eyes, rinse eyes thoroughly with water

• Keep out of reach of children • Do NOT ingest • If swallowed, seek medical help or contact a Poison Control Center right away

DOSAGE AND ADMINISTRATION

Directions • Shake bottle before use • Spray enough product on hands to cover all surfaces • Rub hands together until dry • Adult supervision

Other Information • Do not store bottle above 105°F • May discolor some fabrics • harmful to some wood finishes

INACTIVE INGREDIENT

Inactive Ingredients • Water, isopropyl alcohol, aloe barbadensis, glycerin, natural fragrances, tocophoryl acetate, cellulose

■ LAVENDER ■ PEPPERMINT

MEDICAL

Made in the USA

KILLS MORE THAN 99.9% OF GERMS

FORMULATED FOR PROFESSIONALS

GENTLE ENOUGH FOR EVERYDAY USE

WITH ALOE & VITAMIN E

SKIN MOISTURIZERS

KeriCureMedical.com

® KeriCure Inc • All rights reserved

Distributed by KeriCure Inc 3701A Southwestern Blvd. Baltimore MD 21229